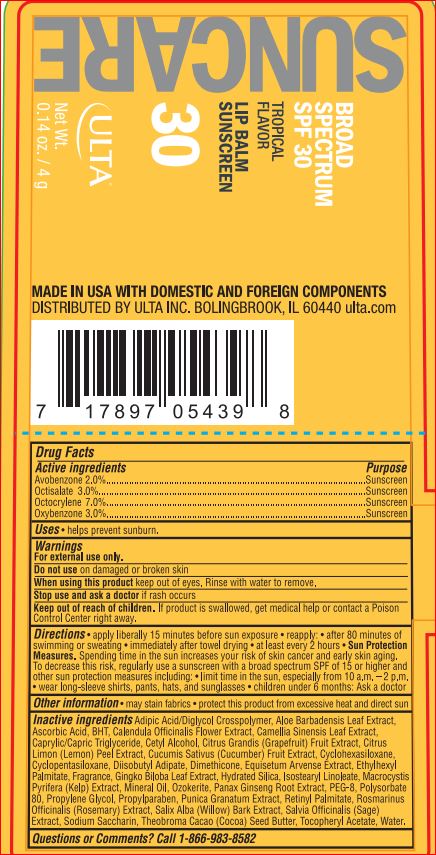 DRUG LABEL: SPF 30 tropical flavor  sunscreen lip balm
NDC: 62296-7780 | Form: STICK
Manufacturer: Ulta
Category: otc | Type: HUMAN OTC DRUG LABEL
Date: 20171012

ACTIVE INGREDIENTS: Avobenzone 2 g/100 g; Octisalate 3 g/100 g; Octocrylene 7 g/100 g; Oxybenzone 3 g/100 g
INACTIVE INGREDIENTS: ADIPIC ACID/DIGLYCOL CROSSPOLYMER (20000 MPA.S); ALOE; Ascorbic Acid; BUTYLATED HYDROXYTOLUENE; CALENDULA OFFICINALIS FLOWER; GREEN TEA LEAF; MEDIUM-CHAIN TRIGLYCERIDES; Cetyl Alcohol; PUMMELO; LEMON PEEL; CUCUMBER; Diisobutyl Adipate; Dimethicone; EQUISETUM ARVENSE BRANCH; Ethylhexyl Palmitate; GINKGO; Hydrated Silica; Isostearyl Linoleate; CERESIN; ASIAN GINSENG; POLYETHYLENE GLYCOL 400; Polysorbate 80; Propylene Glycol; Propylparaben; PUNICA GRANATUM ROOT BARK; VITAMIN A PALMITATE; ROSEMARY; SALIX ALBA BARK; SALVIA OFFICINALIS ROOT; SACCHARIN SODIUM; COCOA BUTTER; .ALPHA.-TOCOPHEROL ACETATE; Trisiloxane; WATER

Drug Facts

Active ingredients Purpose
Avobenzone 2.00%........................................................................Sunscreen
Octisalate 3.00%............................................................................Sunscreen
Octocrylene 7.00%.........................................................................Sunscreen
Oxybenzone 3.00%........................................................................Sunscreen

INDICATIONS AND USAGE

Uses • helps prevent sunburn

Warnings
For external use only
Flammable: Do not use near heat, flame, or while smoking.
Do not use on damaged or broken skin
When using this product • Keep out of eyes. Rinse eyes with water to remove.
• Keep away from face to avoid breathing it • Do not puncture or incinerate.
Contents under pressure. Do not store at temperatures above 120ºF.
Stop use and ask a doctor if rash occurs

Keep out of reach of children. If product is swallowed, get medical help or contact a Poison Control Center right away.

Directions
• apply liberally 15 minutes before sun exposure
• reapply:
• after 80 minutes of swimming or sweating
• immediately after towel drying
• at least every 2 hours
• Sun Protection Measures. Spending time in the sun increases your risk
of skin cancer and early skin aging. To decrease this risk, regularly use
a sunscreen with a broad spectrum SPF of 15 or higher and other
sun protection measures including:
• limit time in the sun, especially from 10 a.m. – 2 p.m.
• wear long-sleeve shirts, pants, hats, and sunglasses
• children under 6 months: Ask a doctor

Inactive ingredients

Ascorbyl Palmitate
Beeswax
BHT
Cetyl Alcohol
Ethylhexyl Palmitate
Euphorbia Cerifera (Candelilla) Wax
Fragrance
Ozokerite
Paraffin
Polyester-8
Polyethylene
Propylparaben
Retinyl Palmitate
Tocopheryl Acetate